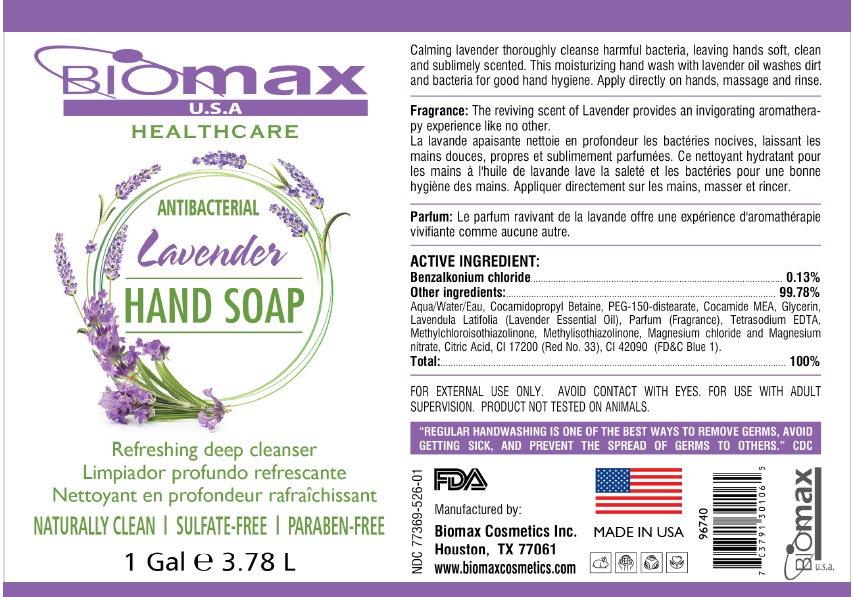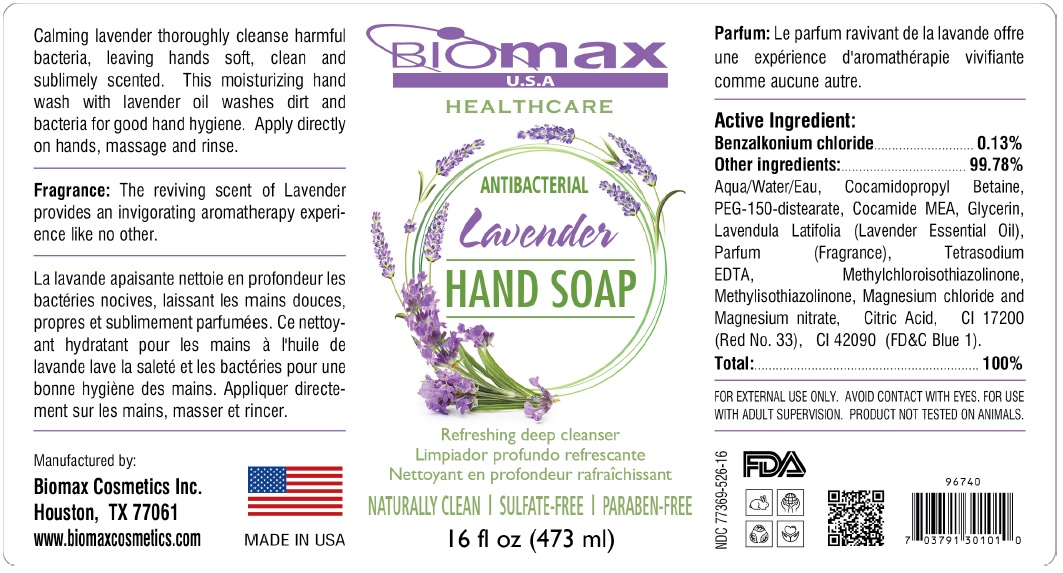 DRUG LABEL: Biomax USA ANTIBACTERIAL HAND WASH
NDC: 77369-526 | Form: SOAP
Manufacturer: Biomax Cosmetics
Category: otc | Type: HUMAN OTC DRUG LABEL
Date: 20200801

ACTIVE INGREDIENTS: BENZALKONIUM CHLORIDE 0.13 g/100 mL
INACTIVE INGREDIENTS: WATER; COCAMIDOPROPYL BETAINE; PEG-150 DISTEARATE; COCO MONOETHANOLAMIDE; GLYCERIN; LAVENDER OIL; EDETATE SODIUM; METHYLCHLOROISOTHIAZOLINONE; METHYLISOTHIAZOLINONE; MAGNESIUM CHLORIDE; MAGNESIUM NITRATE; CITRIC ACID MONOHYDRATE; D&C RED NO. 33; FD&C BLUE NO. 1

Biomax ANTIBACTERIAL Lavender HAND SOAP

Active ingredient:

Benzalkonium chloride..........0.13%

Purpose

Antibacterial

Other ingredients:..............99.78%

Aqua/Water/Eau, Cocamidopropyl Betaine, PEG-150-distearate, Cocamide MEA, Glycerin, , Parfum (Fragrance), Tetrasodium EDTA, Methylchloroisothiazolinone, Methylisothiazolinone, Magnesium chloride and Magnesium nitrate, Citric Acid, CI 17200 (Red No. 33), CI 42090 (FD&C Blue 1).

Uses

• hand sanitizer to decrease bacteria on the skin
• recommended for repeated use

Warnings

FOR EXTERNAL USE ONLY. AVOID CONTACT WITH EYES. FOR USE WITH ADULT SUPERVISION. PRODUCT NOT TESTED ON ANIMALS.

Keep out of reach of children. If swallowed, get medical help or contact a Poison Control Center right away.

Directions

Apply directly on hands, massage and rinse.

HEALTHCARE

Lavender

Refreshing deep cleanser

NATURALLY CLEAN | SULFATE-FREE | PARABEN-FREE

Calming lavender thoroughly cleanse harmful bacteria, leaving hands soft, clean and sublimely scented. This moisuruizing hand wash lavender oil washes dirt and bacteria for good hand hygiene.

Fragrance: The reviving scent of Lavender provides an invigorating aromatherapy experience like no other.

"REGULAR HANDWASHING IS ONE OF THE BEST WAYS TO REMOVE GERMS, AVOID GETTING SICK, AND PREVENT THE SPREAD OF GERMS TO OTHERS." CDC

Manufactured by:

Biomax Cosmetics Inc.

Houston, TX 77061

www.biomaxcosmetics.com

MADE IN USA